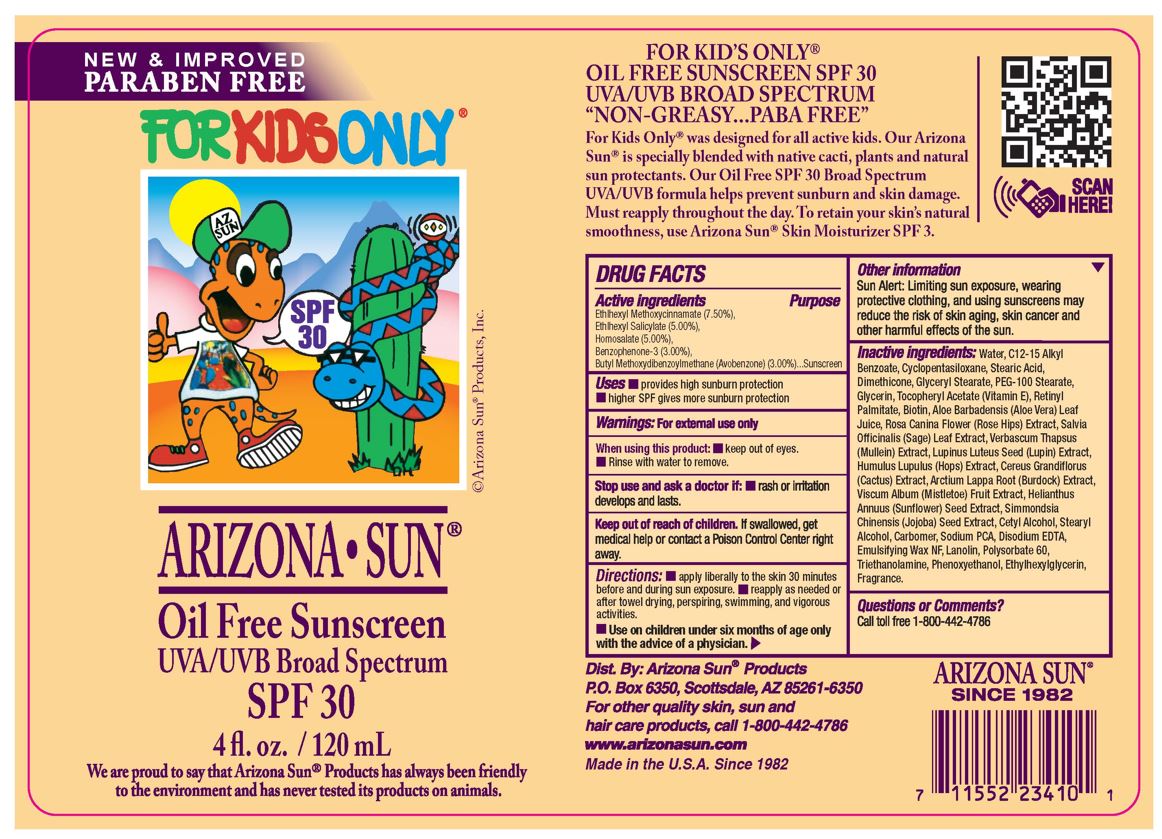 DRUG LABEL: Arizona Sun Kids Sunscreen SPF 30
NDC: 61973-103 | Form: LOTION
Manufacturer: Arizona Sun Products
Category: otc | Type: HUMAN OTC DRUG LABEL
Date: 20240209

ACTIVE INGREDIENTS: OXYBENZONE 30 mg/1 g; OCTISALATE 50 mg/1 g; AVOBENZONE 30 mg/1 g; OCTINOXATE 75 mg/1 g; HOMOSALATE 50 mg/1 g
INACTIVE INGREDIENTS: ALOE VERA LEAF; SAGE; SELENICEREUS GRANDIFLORUS FLOWER; PEG-100 STEARATE; CYCLOMETHICONE 7; STEARIC ACID; DIMETHICONE; MULLEIN LEAF; LUPINUS LUTEUS SEED; ARCTIUM LAPPA ROOT; SUNFLOWER SEED; HOPS; ROSA CANINA FLOWER; VISCUM ALBUM FRUIT; SIMMONDSIA CHINENSIS SEED; STEARYL ALCOHOL; CARBOMER HOMOPOLYMER, UNSPECIFIED TYPE; DISODIUM EDTA-COPPER; GLYCERYL STEARATE SE; GLYCERIN; .ALPHA.-TOCOPHEROL ACETATE; CETYL ALCOHOL; TROLAMINE; PHENOXYETHANOL; ETHYLHEXYLGLYCERIN; WATER; VITAMIN A PALMITATE; BIOTIN; SODIUM PYRROLIDONE CARBOXYLATE; LANOLIN; POLYSORBATE 60; ALKYL (C12-15) BENZOATE

4 oz Arizona Sun Kids SPF 30

Active Ingredients

Ethylhexyl Methoxycinnamate (7.50%), Ethylhexyl Salicylate (5.00%), Homosalate (5.00%), Benzophenone-3 (3.00%), Butyl Methoxydibenzoylmethane (3.00%)

Purpose

Sunscreen

Uses

Provides high sunburn protection. Higher SPF gives more sunburn protection.

Warnings

For external use only

When using this product

keep out of eyes. Rinse with water to remove.

Stop and ask a doctor if

rash or irritation develops and lasts.

Keep out of the reach of children.

If swallowed get medical help or contact a poison control center right away.

Directions

Apply liberally and evenly to the skin 30 minutes before and during sun exposure. Reapply as needed or after towel drying, perspiring, swimming, and vigorous activities. Use on children under six months of age only wih the advise of a physician.

Other Information

Sun Alert: Limiting sun exposure, wearing protective clothing, and using suscreen may reduce the risk of skin aging, skin cancer and other harmful effects of the sun.

Inactive Ingredients

Water, C12-15 Alkyl Benzoate, Cyclopentasiloxane, Stearic Acid, Dimethicone, Glyceryl Stearate, PEG-100 Stearate, Glycerin, Tocopheryl Acetate (Vitamin E), Retinyl Palmitate, Biotin, Aloe Barbadensis (Aloe Vera) Leaf Juice, Rosa Canina Flower (Rose Hips) Extract, Salvia Officinalis (Sage) Leaf Extract, Verbascum Thapsus (Mullein) Extract, Lupinus Luteus Seed (Lupin) Extract, Humulus Lupulus (Hops) Extract, Cereus Grandiflorus (Cactus) Extract, Arctium Lappa Root (Burdock) Extract, Viscum Album (Mistletoe) Fruit Extract, Helianthus Annuus (Sunflower) Seed Extract, Simmondsia Chinensis (Jojoba) Seed Oil, Cetyl Alcohol, Stearyl Alcohol, Carbomer, Sodium PCA, Disodium EDTA,Emulsifying Wax NF, Lanolin, Polysorbate 60, Triethanolamine, Phenoxyethanol, Ethylhexylglycerin, Fragrance.

Questions or Comments?

Call toll free 1-800-442-4786